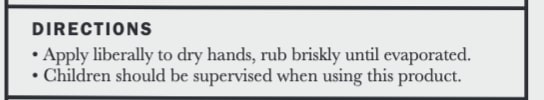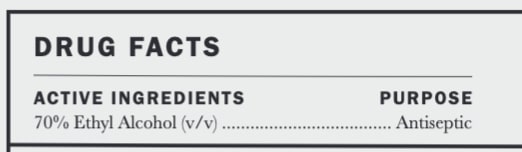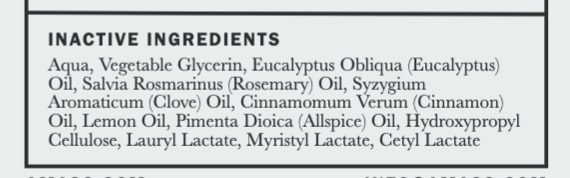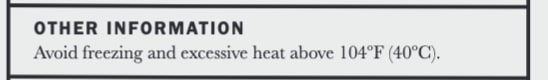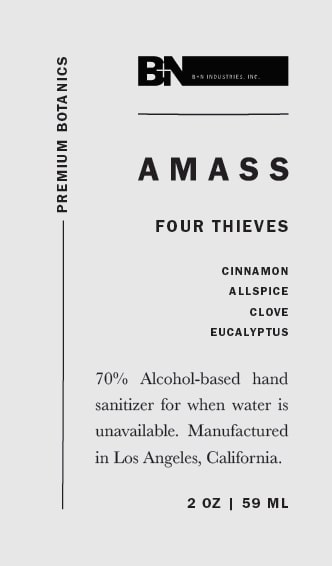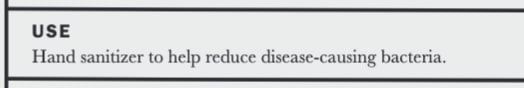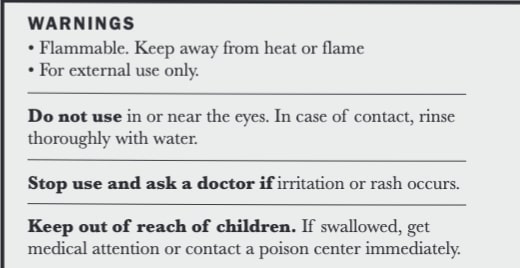 DRUG LABEL: AMASS Four Thieves Sanitizer Serum
NDC: 77419-2001 | Form: GEL
Manufacturer: AMASS Brands, Inc
Category: otc | Type: HUMAN OTC DRUG LABEL
Date: 20200903

ACTIVE INGREDIENTS: ALCOHOL 347.655 mL/473 mL
INACTIVE INGREDIENTS: GLYCEROL FORMAL 7.095 mL/473 mL; CLOVE OIL 0.06103225806 mL/473 mL; CINNAMON OIL 0.4882580645 mL/473 mL; LEMON OIL 0.2441290323 mL/473 mL; ALLSPICE OIL 0.2441290323 mL/473 mL; ROSEMARY OIL 0.06103225806 mL/473 mL; EUCALYPTUS OIL 2.685419355 mL/473 mL; MYRISTYL LACTATE 1.576666667 mL/473 mL; HYDROXYPROPYL CELLULOSE (90000 WAMW) 2.365 mL/473 mL; WATER 107.371 mL/473 mL; CETYL LACTATE 1.576666666 mL/473 mL; LAURYL LACTATE 1.576666667 mL/473 mL

Active Ingredients ......... Purpose
70% Ethyl Alcohol (v/v)........ Antiseptic

Do not use in or near the eyes. In case of contact, rinse thoroughly with water.

USE
Hand sanitizer to help reduce disease-causing bacteria

Keep out of reach of children. If swallowed, get medical attention or contact a poison center immediately.

Stop use and ask a doctor if irriation or rash occurs.

Directions
Apply liberally to dry hands, rub briskly until evaporated
Children should be supervised when using this product

OTHER INFORMATION
Avoid freezing and excessive heat above 104F (40C)

WARNINGS
Flammable. Keep away from heat or flame.
For external use only.
Do not use in or near the eyes. In case of contact, rinse thoroughly with water.
Stop use and ask a doctor if irritation or rash occurs.
Keep out of reach of children. IF swallowed, get medical attention or contact a poison center immediately.

DIRECTIONS
Apply liberally to dry hands, rub briskly until evaporated.
Children should be supervised when using this product

Inactive ingredients

Aqua, Vegetable Glycerin, Eucalyptus Obliqua (Eucalyptus) Oil, Salvia Rosmarinus (Rosemary) Oil, Syzygium Aromaticum (Clove) Oil, Cinnamomum Verum (Cinnamon) Oil, Lemon Oil, Pimenta Dioica (Allspice) Oil, Hydroxypropyl Cellulose, Lauryl Lactate, Myristyl Lactate, Cetyl Lactate

DIRECTIONS
Apply liberally to dry hands, rub briskly until evaporated.
Children should be supervised when using this product

WARNINGS
Flammable. Keep away from heat or flame.
For external use only.
Do not use in or near the eyes. In case of contact, rinse thoroughly with water.
Stop use and ask a doctor if irritation or rash occurs.
Keep out of reach of children. IF swallowed, get medical attention or contact a poison center immediately.

USE
Hand sanitizer to help reduce disease-causing bacteria.

PACKAGE LABEL

BN Logo

AMASS Logo

FOUR THIEVES

CINNAMON

ALLSPICE

CLOVE

EUCALYPTUS

70% Alcohol-based hand sanitizer for when water is unavailable. Manufactured in Los Angeles, California

2 oz | 59 mL

------------------Premium Botanics